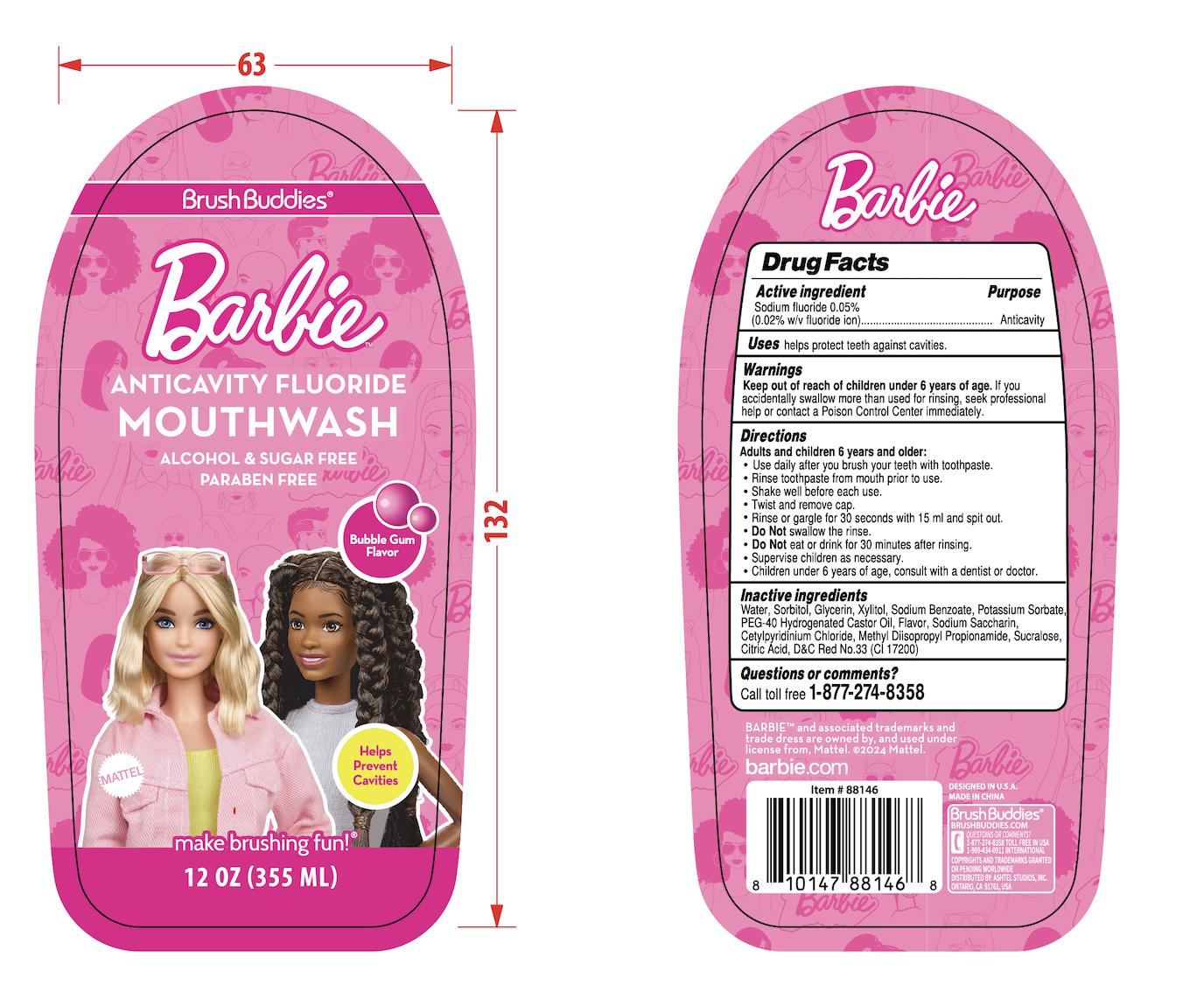 DRUG LABEL: BRUSH BUDDIES BRBIE ANTICAVITY FLUORIDE BUBBLEGUM
NDC: 73928-048 | Form: LIQUID
Manufacturer: Kingkey MBC Life Technology Group co., LTD.
Category: otc | Type: HUMAN OTC DRUG LABEL
Date: 20251211

ACTIVE INGREDIENTS: SODIUM FLUORIDE 0.05 g/100 mL
INACTIVE INGREDIENTS: CETYLPYRIDINIUM CHLORIDE; POLYOXYL 40 HYDROGENATED CASTOR OIL; SUCRALOSE; SACCHARIN SODIUM; CITRIC ACID MONOHYDRATE; SORBITOL; METHYL DIISOPROPYL PROPIONAMIDE; WATER; POTASSIUM SORBATE; GLYCERIN; XYLITOL; D&C RED NO. 33; SODIUM BENZOATE

73928-048 BRUSH BUDDIES BRBIE ANTICAVITY FLUORIDE BUBBLEGUM(0.05%)

Active ingredient

SODIUM FLUORIDE 0.05%

Purpose

(0.02% w/v fluoride ion)---------Anticavity

Warnings

Keep out of reach of children under 6 years of age.lf you accidentally swallow more than used for rinsing, seek professional help or contact a Poison Control Center immediately.

Directions

Adults and children 6 years and older:

- Use daily after you brush your teeth with toothpaste
- Rinse toothpaste from mouth prior to use.
- Shake well before each use.
- Twist and remove cap.
- Rinse or gargle for 30 seconds with 15 ml and spit out
- Do Notswallow the rinse.
- Do Noteat or drink for 30 minutes after rinsing Supervise children as necessary.
- Children under 6 years of age, consult with a dentist or doctor.

Keep out of reach of children under 6 years of age, lf youaccidentally swallow more than used for rinsing, seek professionahelp or contact a Poison Control Center immediately.

Uses

helps protect teeth against cavities.

Inactive ingredients

WATER
SORBITOL
GLYCERIN
XYLITOL

SODIUM BENZOATE
POTASSIUM SORBATE
PEG-40 HYDROGENATED CASTOR OIL
FLAVOR
SODIUM SACCHARIN
CETYLPYRIDINIUM CHLORIDE

METHYL DIISOPROPYL PROPIONAMIDE
SUCRALOSE
CITRIC ACID

D&C Red No.33（CI 17200）